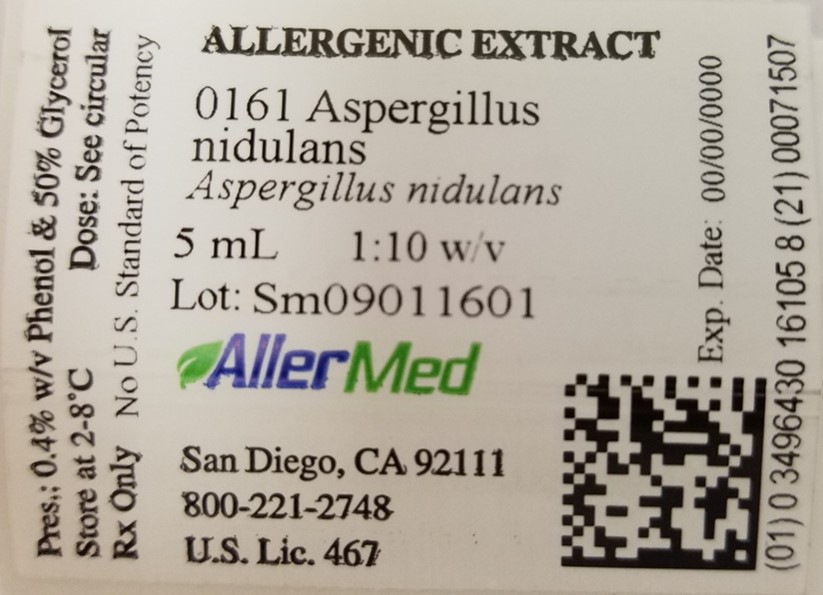 DRUG LABEL: Beech Pollen
NDC: 49643-349 | Form: INJECTION
Manufacturer: Allermed Laboratories, Inc.
Category: other | Type: NON-STANDARDIZED ALLERGENIC LABEL
Date: 20250603

ACTIVE INGREDIENTS: FAGUS GRANDIFOLIA POLLEN 0.05 g/1 mL
INACTIVE INGREDIENTS: SODIUM CHLORIDE 0.0025 g/1 mL; SODIUM BICARBONATE 0.00125 g/1 mL; GLYCERIN 0.53 g/1 mL; PHENOL 0.004 g/1 mL; WATER

ALLERGENIC EXTRACT INSTRUCTIONS FOR USE AND DOSAGE SCHEDULE

WARNINGS

This allergenic product is intended for use by physicians who are experienced in the administration of allergenic extracts, and the emergency care of anaphylaxis, or for use under the guidance of an allergy specialist.
This allergenic extract is not directly interchangeable with other allergenic extracts. The initial dose must be based on skin testing as described in the dosage and administration section of this insert. Patients being switched from other types of extracts, such as alum precipitated extracts, should be started as though they were coming under treatment for the first time. Patients should be instructed to recognize adverse reaction symptoms and cautioned to contact the physician's office if reaction symptoms occur. As with all allergenic extracts, severe systemic reactions may occur. In certain individuals these systemic reactions may occur. In certain individuals these reactions may be life threatening. Patients should be observed for at least 20 minutes following treatment, and emergency measures as well as personnel trained in their use should be immediately available in the event of a life threatening reaction.
This product should not be injected intravenously (see Dosage and Administration). Refer also to the Warnings, Precautions, Adverse Reactions and Overdosage sections below.

DESCRIPTION

Allergenic extract contains the aqueous extractables from allergenic source material in extracting solution containing 0.25% sodium chloride, 0.125% sodium bicarbonate, and 50% glycerol. 0.4% phenol is added as a preservative. The weight by volume value shown on the label is a measurement of extract concentration, rather than extract potency. Extracts for which U.S. standards exist are labeled in allergy units, in addition to w/v strength.

CLINICAL PHARMACOLOGY

Positive skin tests with allergenic extract are the result of histamine release from mast cells sensitized with allergen specific IgE. The exact mechanisms by which immunotherapy relieves symptoms of allergy are still under investigation. Elevations in allergen-specific IgG antibodies and an increase in the activity of T suppressor lymphocytes appear to be some of the immunologic changes that occur from hyposensitization. (1,2,3)

INDICATIONS AND USAGE

Allergenic extract may be used as a diagnostic skin test reagent in persons suspected of being sensitive to the allergenic source material from which the extract is made. Skin tests should be used in conjunction with a thorough allergic history to establish the relevance of a given allergen in the etiology of allergic disease. (4,5,6)
Immunotherapy with allergenic extract is indicated in persons suffering from allergic rhinitis, bronchitis, conjunctivitis, urticaria and asthma. The therapeutic efficacy of allergenic extract has been proven in ragweed, grass, and mountain cedar pollinosis, cat-induced asthma and hypersensitivity to hymenoptera venoms. (7-12)

Immunotherapy may be used along with or exclusive of antihistamines and other medications used to control allergic symptoms.

CONTRAINDICATIONS

Allergenic extract should not be administered to a non-allergic person. However, there are no absolute contraindications to the use of allergenic extract for treatment in appropriate individuals. Relative contraindications include: EXTREME SENSITIVITY TO AN ALLERGEN - Determined from the allergic history, or from previous anaphylaxis following skin testing or subcutaneous injection; AUTOIMMUNE DISEASE - Individuals with autoimmune disease may be at risk, due to the possibility of routine immunizations exacerbating symptoms of the underlying disease; PREGNANCY - In limited controlled studies of women receiving allergenic extract during conception and throughout all trimesters of pregnancy, no evidence was found that extract is harmful to the fetus or mother. However, because of the known pharmacologic action of histamine on uterine muscle, any treatment that might result in the release of significant amounts of this mediator should be avoided if possible (13). See Precaution #4; MYOCARDIAL INFARCTION - Patients who have experienced a recent myocardial infarction may not be able to tolerate immunotherapy. As in all of the above circumstances, the benefit to risk ration must be carefully evaluated; BLEEDING DIATHESIS - Patients with a bleeding tendency should not be tested or treated with allergenic extract, unless the physician responsible believes that such procedures are safe to perform.
Allergenic extract should be temporarily withheld from patients if any of the following conditions exist: (1) severe symptoms of hay fever and/or asthma; (2) infection or flu accompanied by fever; and (3) exposure to excessive amounts of clinically relevant allergens prior to skin testing or immunotherapy.

WARNINGS

The only approved method approved for determining hypersensitivity to Allermed Laboratories Allergenic Extracts is by diagnostic skin testing (See DOSAGE AND ADMINISTRATION - DIAGNOSIS).

Physicians who administer allergenic extrract should have emergency medication and equipment available to treat anaphylaxis (14). See Precautions, Adverse Reactions and Overdosage below.

To reduce the risk of anaphylaxis, the following measures must be observed.

1. Concentrated extract must be diluted before use for intradermal skin testing and for beginning immunotherapy. It should never be in injected intravenously during testing or treatment procedures.

2. Patients who are highly sensitive, determined from clinical findings and test results, may require that treatment start with a very weak concentration of extract, such as 1:10,000,000 v/v.

3. The dosage of fresh (new) extract given to a patient receing maintenance injections must be reduced to one-fourth the amount given from the previous (old) lot (See Immunotherapy, last paragraph).

4. Patients who are transferred to standardized extract after previous treatment with unstandardized extract must bew skin tested with serial dilutions, starting with a 1:100,000 v/v dilution of hte standardized extract, to determine a safe, non-reacting starting dose.

5. Patients who are transferred to this extract treatment with alum precipiated or other modified extract must re-start injections with the beginning recommended dose of this extract.

PRECAUTIONS

1. Extract should be stored at 2°C to 8°C since higher temperatures may adversely affect the stability of the product. Do not freeze.
2. After the needle is inserted subcutaneously, the plunger should be withdrawn slightly to check for the presence of blood in the syringe. If blood is observed, a new injection should be prepared and given at another site, observing the same precautions.
3. Treatment with beta-blocking drugs may make patients refractory to the usual dose of epinephrine, in the event epinephrine is required to control an adverse allergic reaction.
4. PREGNANCY CATEGORY C. Allergenic extract. Animal reproduction studies have not been conducted with allergenic extract. It is also not known whether allergenic extract can cause fetal harm when administered to a pregnant woman or can affect reproduction capacity. Allergenic extract should be given to a pregnant woman only if clearly needed.
5. PATIENT INSTRUCTIONS: Patients should be instructed to remain in the physician's office for at least 20 minutes after skin testing and after each treatment injection, and immediately notify the physician if symptoms of a generalized reaction or shock occur.
6. CARCINOGENESIS, MUTAGENESIS, IMPAIRMENT OF FERTILITY: Long term studies have not been conducted with allergenic extracts to determine their potential for carcinogenesis, mutagenesis, and impairment of fertility.
7. LACTATION: Data are not available on the secretion of allergenic extract in human milk and it is not known what affect this might have on the nursing infant.
8. PEDIATRIC USE: The dose of allergenic extract recommended for children is the same as that used for adults, except in the injection of large doses of extract for treatment. In this case, the amount of extract given to a child may be modified so that the discomfort of the injection is minimized.

ADVERSE REACTIONS

Local Reactions: The occurrence of a hive 5 to 15 minutes after the subcutaneous injection of extract does not require a reduction in dosage. However, a local reaction with edema larger than 2 cm in diameter or swelling and redness that persist for several hours or longer indicates that too much extract has been given. Treatment should be altered as follows:

1. Additional injections should not be given until all evidence of the reaction has disappeared.
2. The next injection administered should be 50% of the last non-reacting dose or less, depending upon the size and severity of the local reaction.
3. Subsequent injections should be continued at the reduced dosage unless the physician responsible for treatment believes that it is safe to increase the dose, and that possible clinical improvement would result form the administration of a larger dose of extract.

Systemic Reactions:Systemic (generalized) reactions may range from a mild exacerbation of the patient's allergic symptoms to hives, anaphylactic shock, or even death from anaphylaxis. The reaction usually occurs 5 to 20 minutes after injection. As a rule, the more quickly a reaction develops, the more serious it is likely to become. Symptoms may include sneezing, coughing, itching, shortness of breath, abdominal cramps, vomiting, diarrhea, tachycardia, hypotension and respiratory failure in severe cases. The reaction is usually stopped by the subcutaneous injection of Epinephrine HCL 1:1,000 (See Overdosage below). The oral administration of antihistamines and the placement of a tourniquet proximal to the injection site are helpful adjuncts. In the event that additional measures are required, it may be necessary to treat the patient for BRONCHOSPASM with intravenous aminophylline, intravenous fluids and corticosteroids; for HYPOTENSION with vasopressors, volume repletion, isoproterenol and corticosteroids; for LARYNGEAL OBSTRUCTION with oxygen and tracheostomy and for CARDIAC ARREST with cardiopulmonary resuscitation and other appropriate measures.
Immunotherapy after anaphylaxis should be continued if the cause of the reaction can be identified and appropriate precautions taken to insure that a subsequent reaction does not occur.

OVERDOSAGE

A strong local reaction to the injection of extract may be treated with oral antihistamines and the local application of a cold compress. The dosage must be reduced and additional extract must not be given until all evidence of the reaction has disappeared.
A systemic reaction following the injection of extract must be treated immediately as follows (Ref. #4, vol. 2, p. 888):

1. 0.01 mL/kg up to 0.2 mL of aqueous epinephrine HCl 1:1000 subcutaneously at the injection site of antigen.
2. 0.01 mL/kg up to 0.3 mL of aqueous epinephrine HCl 1:1000 subcutaneously at another site.
3. Diphenhydramine intravenously or intramuscularly, 1.25 mg/kg up to 50 mg.
4. Tourniquet above the injection site of antigen.

Specific reactions:

1. Brochospasm: intravenous aminophylline 4 mg/kg up to 500 mg given over 10 to 15 minutes, aqueous hydrocortisone 5 mg/kg up to 200 mg, oxygen.
2. Laryngeal edema: oxygen, intubation, tracheostomy.
3. Hypotension: vasopressors, fluids, corticosteroids.
4. Cardiac arrest: resuscitation, sodium bicarbonate, defibrillation, antiarrhythmia medications.

DOSAGE AND ADMINISTRATION

Diagnosis: Concentrated extract may be used for scratch or prick testing providing the patient is not extremely sensitive. In this case, the extract should be diluted 10 fold before a scratch or prick test is performed. Extract for intradermal testing must be used as follows:
a. Patients with positive scratch or prick tests: It is not advisable to perform an intradermal skin test if the patient has a positive scratch or prick test.

b. Patients with a negative scratch or prick test: Patients who do not react to a valid scratch or prick test should be tested intradermally with 0.05 mL of a 1:1000 v/v dilution of the concentrate. If the test is negative, a second test should be performed with 0.05 mL of a 1:100 v/v dilution of concentrate.

c. Patients tested only by the intradermal method: Patients suspected of being highly allergic should be tested with 0.05 mL of a 1:100,000 v/v dilution of the concentrate. A negative test should be followed by repeat tests using 10 fold stronger concentrations until the maximum dose of 0.05 mL of a 1:100 v/v dilution is reached.
Interpretation of Results
Scratch and Prick Test
A negative test shows only a slight red area at the site of scarification or prick penetration. Positive tests are scored as follows:
1+ Erythema with 5 mm wheal
2+ Erythema with a 5-10 mm wheal
3+ Erythema with a 10-15 mm wheal
4+ Erythema with a wheal 15 mm (or larger) with pseudopodia
Intradermal Test
A negative test shows no change in the appearance and size of the 5 mm wheal created by the I.D. injection of 0.05 mL of extract. Positive tests are scored as follows:
1+ Erythema 10-20 mm with a 5-10 mm wheal
2+ Erythema 20-30 mm with a 5-10 mm wheal
3+ Erythema 30-40 mm with a 10-15 mm wheal
4+ Erythema greater than 40 mm with a 15 mm wheal (or larger) with pseudopodia
Immunotherapy
Allergenic extract should be administered subcutaneously in the outer aspect of the upper arm using a sterile tuberculin syringe and needle. The skin should be cleaned with 70% alcohol and aseptic technique should be observed in removing the extract from the vial. Care must be taken to avoid injecting the extract into a blood vessel because of the risk of anaphylaxis.
Concentrated extract must be diluted before administration to new patients. A 1:100,000 v/v dilution of concentrate is usually satisfactory to start treatment. However, as a precaution against overdose, a skin test with the intended starting dose should be done to help evaluate the patient's sensitivity to the product. If the skin response is larger than 5 mm edema/15 mm erythema, the extract is too strong and must be diluted before it is given subcutaneously. The doses shown in the Suggested Dosage Schedule below are recommended unless the patient's skin test response and allergic history indicates that more dilute extract should be used.
Little is known about the required accumulated dosage of allergen that is needed to relieve symptoms. However, studies have shown that high dose immunotherapy is efficacious in the treatment of allergic rhinitis and asthma. For this reason, treatment with extract from Vial #5 is recommended, providing the patient can tolerate the extract without experiencing local or systemic reactions. Treatment with Vial #6 may be used for patients who have not had adverse reactions to extract in Vial #5 and who require more concentrated extract to control or relieve symptoms.
Patients who have received allergenic extract for maintenance therapy SHOULD NOT be given the same dose from a fresh vial of extract. IT IS ADVISABLE TO REDUCE THE DOSAGE OF FRESH EXTRACT TO ONE-FOURTH THE AMOUNT GIVEN FROM A PREVIOUS LOT OF EXTRACT MADE AT THE SAME CONCENTRATION AND BY THE SAME FORMULA.

Suggested Dosage Schedule
No. | Vial #1 1:100,000 w/v frequency twice weekly mL | Vial #2 1:10,000 w/v frequency twice weekly mL | Vial #3 1:1,000 w/v frequency once weekly mL | Vial #4 1:100 w/v frequency once weekly mL | Vial #5 1:10 w/v frequency every two-four weeks mL | Vial #6 Concentrate frequency every two-four weeks mL
1 | 0.025 | 0.025 | 0.025 | 0.025 | 0.025 | 0.025
2 | 0.05 | 0.05 | 0.05 | 0.05 | 0.05 | 0.05
3 | 0.10 | 0.10 | 0.10 | 0.10 | 0.10 | 0.10
4 | 0.15 | 0.15 | 0.15 | 0.15 | 0.15 | 0.15
5 | 0.20 | 0.20 | 0.20 | 0.20 | 0.20 | 0.20
6 | 0.25 | 0.25 | 0.25 | 0.25 | 0.25 | -
7 | 0.30 | 0.30 | 0.30 | 0.30 | 0.30 | -

HOW SUPPLIED

Allergenic extract is supplied in 5 mL dropper vials for scratch or prick testing and in 10, 30, and 50 mL vials for bulk use.

STORAGE AND HANDLING

Extract should be stored at 2-8°C since higher temperatures may adversely affect stability. Do not freeze.

REFERENCES

1. Levy, D.A., Lichtenstein, L.M., Goldstein, E.O. and Ishizaka, K. Immunologic and cellular changes accompanying the therapy of pollen allergy. J. Clinical Investigations. 50:360, 1971.
2. Evans, R., Pence, H., Kaplan, H., and Rocklin, R. The effect of immunotherapy on humoral and cellular response in ragweed hayfever. J. Clinical Investigations. 57:1378, 1976.
3. Ishizaka, K. Cellular events in the IgE antibody response. Adv. In Immunology. 23:50, 1976.
4. Middleton, Elliott Jr., Reed, C.E. and Ellis, E.F. (Eds.) Allergy, Principles and Practice Vols. 1 & 2, C.V. Mosby 1978.
5. Sheldon, J.M., Lovell, R.G. and Matthews, K.P. A Manual of Clinical Allergy. W.B. Saunders, 1967.
6. Nelson, H.S. Diagnostic procedures in allergy. I. Allergy skin testing. Ann. Allergy. 51:411, 1983.
7. Norma, P.S., Winkenwerder, W.L., and Lichtenstein, L.M. Immunotherapy of hay fever with ragweed antigen E: comparisons with whole pollen extract and placebos. J. Allergy. 42:93, 1968.
8. Milner, F.H. and Tees, E.C. Specific sensitivity to individual grass pollens in some hay fever patients. Clinical Allergy. 2:83, 1972.
9. Frankland, A.W. and Augustine, R. Grass pollen antigens effective in treatment. Clinical Science. 23:95, 1962.
10. Pence, H.L., Mitchell, D.Q., Greely, R.L., Updegraff, B.R. and Selfridge, H.A. Immunotherapy for mountain cedar pollinosis: a double-blind controlled study. J. Allergy ad Clinical Immunology. 58:39, 1976.
11. Taylor, W.W., Ohman, J.L. Jr. and Lowell, F.C. Immunotherapy in cat- induced asthma. Double-blind trial with evaluation of bronchial responses to cat allergen and histamine. J. Allergy and Clinical Immunology. 61:283. 1978.
12. Lichtenstein, L.M., Valentine, M.D. and Sobotka, A.K. Insect allergies. The state of the art. J. Allergy and Clinical Immunology. 61:268, 1978.
13. Metzger, W.J., Turner, E., and Patterson, R. The safety of immunotherapy during pregnancy. J. Allergy and Clinical Immunology. 61:268. 1978.
14. Ouellette, J.J. Emergency management of allergic reactions. Modern Medicine 99, 1975.